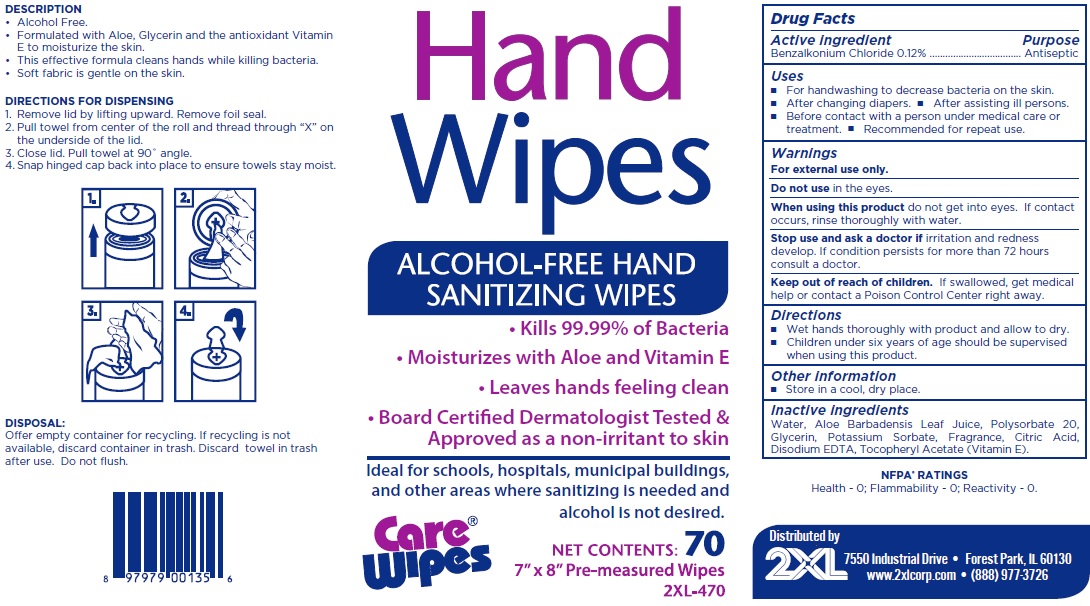 DRUG LABEL: Care wipes 70 hand wipes
NDC: 71995-001 | Form: CLOTH
Manufacturer: 2XL Corporation
Category: otc | Type: HUMAN OTC DRUG LABEL
Date: 20210616

ACTIVE INGREDIENTS: BENZALKONIUM CHLORIDE 1.2 mg/1 mL
INACTIVE INGREDIENTS: WATER; ALOE VERA LEAF; POLYSORBATE 20; GLYCERIN; POTASSIUM SORBATE; CITRIC ACID MONOHYDRATE; EDETATE DISODIUM ANHYDROUS; .ALPHA.-TOCOPHEROL ACETATE

Care wipes 70 hand wipes

Active ingredient

Benzalkonium Chloride 0.12%

Purpose

Antiseptic

Uses

- For handwashing to decrease bacteria on the skin.
- After changing diapers.
- After assisting ill persons.
- Before contact with a person under medical care or treatment.
- Recommended for repeated use.

Warnings

For external use only.

Do not use

in the eyes.

When using this product

do not get into eyes. If contact occurs, rinse thoroughly with water.

Stop use and ask doctor if

irritation and redness develop. If condition persists for more than 72 hours consult a doctor.

Keep out of reach of children.

If swallowed, get medical help or contact a Poison Control Center right away.

Directions

- Wet hands thoroughly with product and allow to dry.
- Children under six years of age should be supervised when using this product.

Other information

- Store in a cool, dry place.

Inactive ingredients

Water, Aloe Barbadensis Leaf Juice, Polysorbate 20, Glycerin, Potassium Sorbate, Fragrance, Citric Acid, Disodium EDTA, Tocopheryl Acetate (Vitamin E).